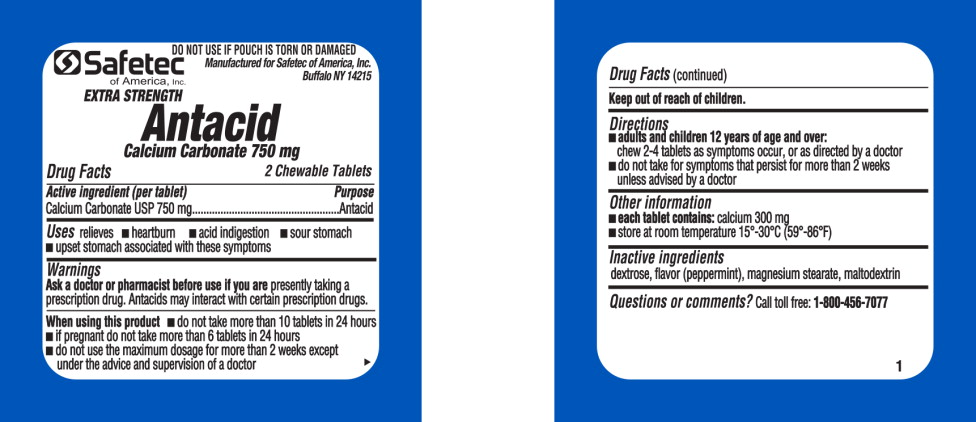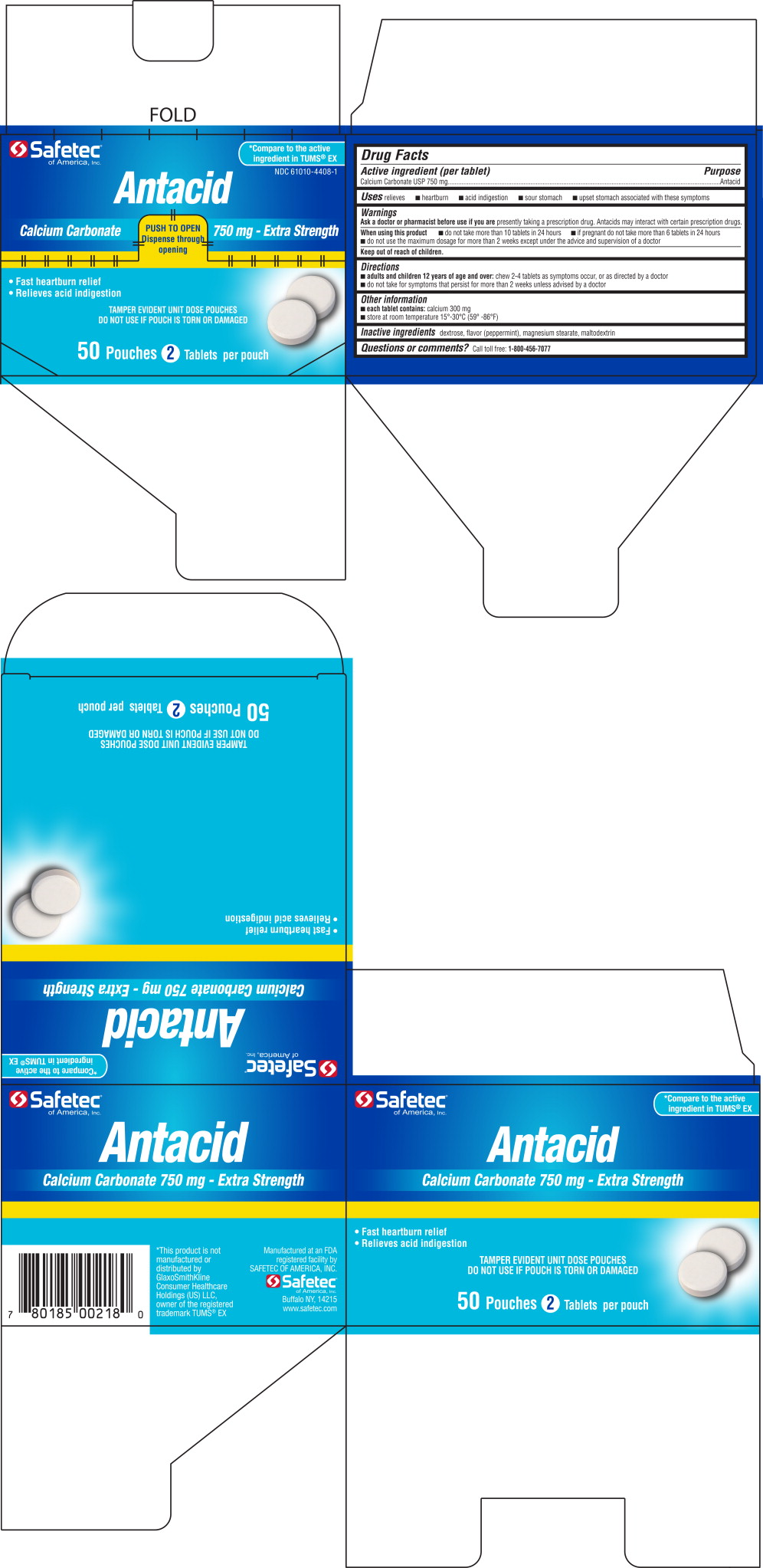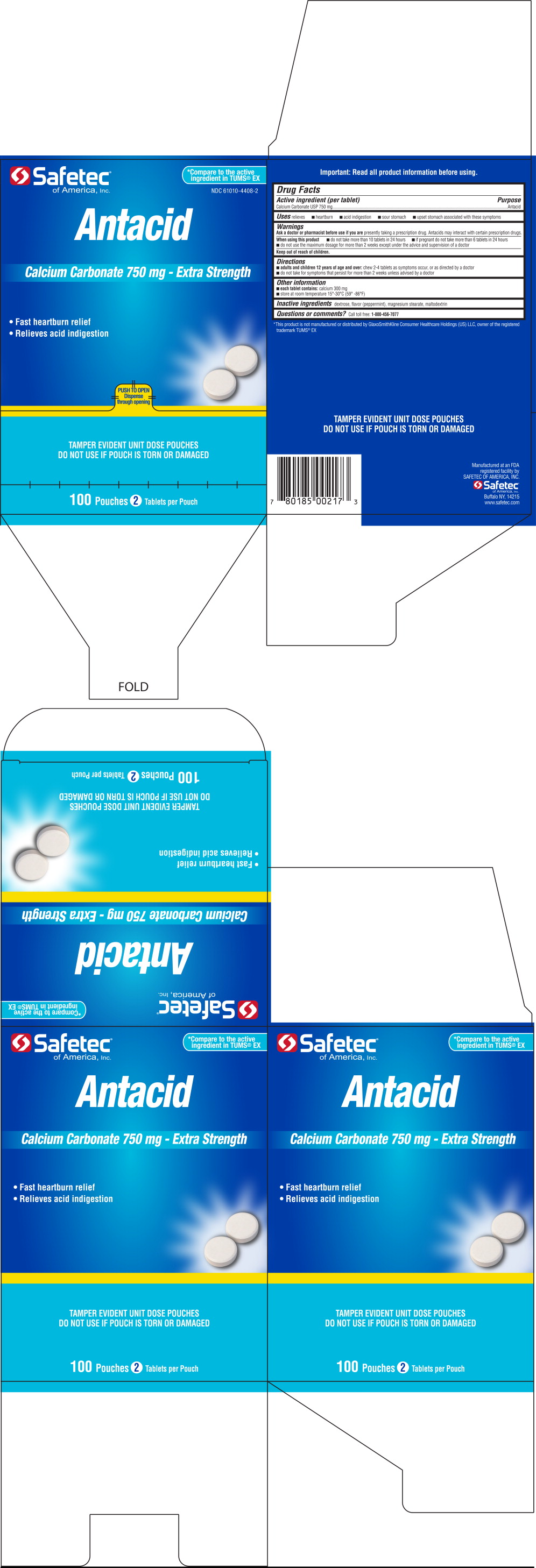 DRUG LABEL: Antacid
NDC: 61010-4408 | Form: TABLET
Manufacturer: Safetec of America, Inc.
Category: otc | Type: HUMAN OTC DRUG LABEL
Date: 20191230

ACTIVE INGREDIENTS: CALCIUM CARBONATE 750 mg/1 1
INACTIVE INGREDIENTS: DEXTROSE; MAGNESIUM STEARATE; MALTODEXTRIN; PEPPERMINT

Drug Facts

Active ingredient (per tablet)

Calcium Carbonate USP 750 mg

Purpose

Antacid

INDICATIONS AND USAGE

Uses relieves

- heartburn
- acid indigestion
- sour stomach
- upset stomach associated with these symptoms

Warnings

Ask a doctor or pharmacist before use if you are presently taking a prescription drug. Antacids may interact with certain prescription drugs.

When using this product

- do not take more than 10 tablets in 24 hours
- if pregnant do not take more than 6 tablets in 24 hours
- do not use the maximum dosage for more than 2 weeks except under the advice and supervision of a doctor

Directions

Keep out of reach of children.

- adults and children 12 years of age and over: chew 2-4 tablets as symptoms occur, or as directed by a doctor
- do not take for symptoms that persist for more than 2 weeks unless advised by a doctor

Other information

- each tablet contains: calcium 300 mg
- store at room temperature 15°-30°C (59°-86°F)

Inactive ingredients

dextrose, flavor (peppermint), magnesium stearate, maltodextrin

Questions or comments?

Call toll free: 1-800-456-7077

Principal Display Panel - 750 mg Pouch Label

Safetec
of America, Inc.

DO NOT USE IF POUCH IS TORN OR DAMAGED

Manufactured for Safetec of America, Inc.
Buffalo NY 14215

EXTRA STRENGTH

Antacid

Calcium Carbonate 750 mg

2 Chewable Tablets

Principal Display Panel – 50 Count Carton

Safetec®
of America, Inc.

*Compare to the active
ingredient in TUMS® EX

NDC 61010-4408-1

Antacid

Calcium Carbonate 750 mg – Extra Strength

- Fast heartburn relief
- Relieves acid indigestion

TAMPER EVIDENT UNIT DOSE POUCHES

DO NOT USE IF POUCH IS TORN OR DAMAGED

50 Pouches 2 Tablets per pouch

Principal Display Panel – 100 Count Carton

Safetec®
of America, Inc.

*Compare to the active
ingredient in TUMS® EX

NDC 61010-4408-2

Antacid

Calcium Carbonate 750 mg – Extra Strength

- Fast heartburn relief
- Relieves acid indigestion

PUSH TO OPEN

Dispense
through opening

TAMPER EVIDENT UNIT DOSE POUCHES

DO NOT USE IF POUCH IS TORN OR DAMAGED

100 Pouches 2 Tablets per pouch